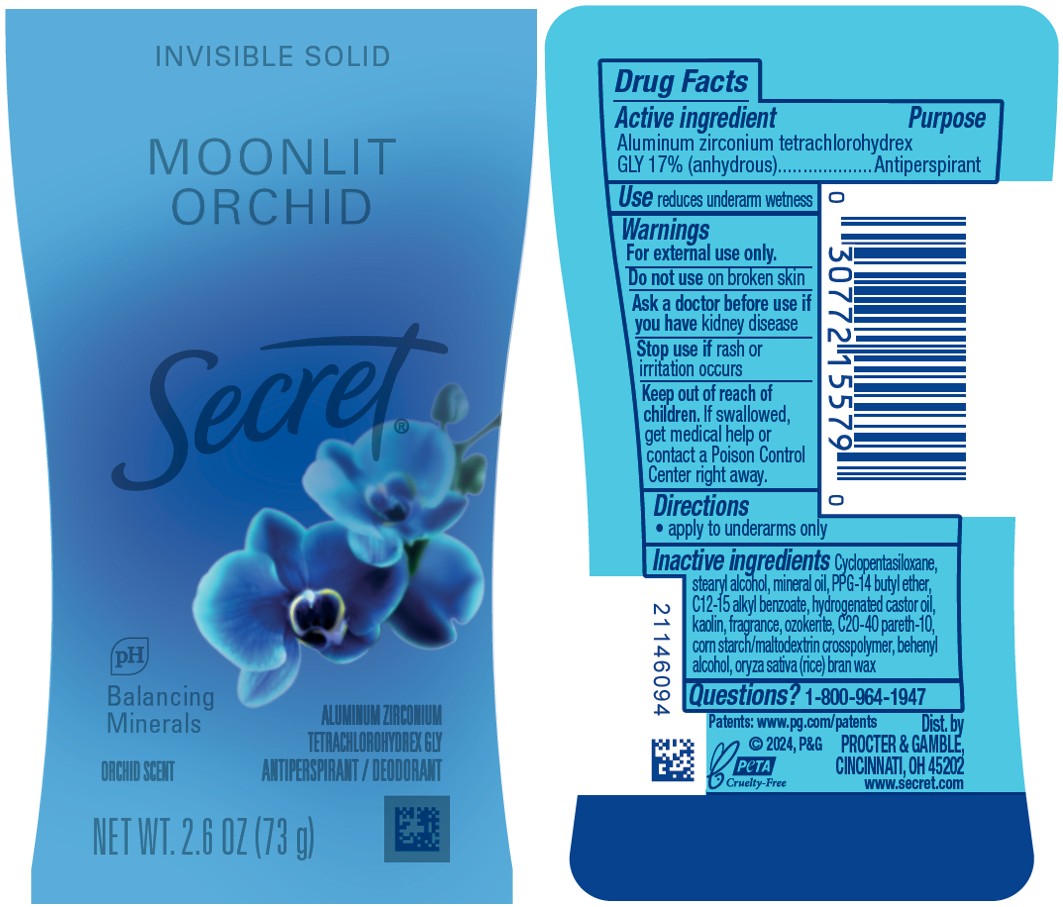 DRUG LABEL: Secret Moonlit Orchid Invisible
NDC: 84126-201 | Form: STICK
Manufacturer: The Procter & Gamble Manufacturing Company
Category: otc | Type: HUMAN OTC DRUG LABEL
Date: 20251119

ACTIVE INGREDIENTS: ALUMINUM ZIRCONIUM TETRACHLOROHYDREX GLY 17 g/100 g
INACTIVE INGREDIENTS: ORYZA SATIVA (RICE) BRAN; C20-40 PARETH-10; HYDROGENATED CASTOR OIL; CYCLOPENTASILOXANE; STEARYL ALCOHOL; PPG-14 BUTYL ETHER; KAOLIN; MINERAL OIL; BEHENYL ALCOHOL; C12-15 ALKYL BENZOATE; CERESIN

Secret Moonlit Orchid Invisible Solid

Drug Facts

Active ingredient

Aluminum zirconium tetrachlorohydrex Gly 17% (anhydrous)

Purpose

Antiperspirant

Use

reduces underarm wetness

Warnings

For external use only.

Do not use on broken skin

Ask a doctor before use if you have kidney disease

Stop use if rash or irritation occurs

Keep out of reach of children. If swallowed, get medical help or contact a Poison Control Center right away.

Directions

- apply to underarms only

Inactive ingredients

Cyclopentasiloxane, stearyl alcohol, mineral oil, PPG-14 butyl ether, C12-15 alkyl benzoate, hydrogenated castor oil, kaolin, fragrance, ozokerite, C20-40 pareth-10, corn starch/maltodextrin crosspolymer, behenyl alcohol, oryza sativa (rice) bran wax

Questions?

1-800-964-1947

Dist. by PROCTER & GAMBLE,
CINCINNATI, OH 45202.

PRINCIPAL DISPLAY PANEL - 73 g Canister Label

INVISIBLE SOLID

MOONLIT

ORCHID

Secret

pH Balancing Minerals

ALUMINUM ZIRCONIUM TETRACHLOROHYDREX GLY

ANTIPERSPIRANT / DEODORANT

NET WT. 2.6 OZ (73 g)